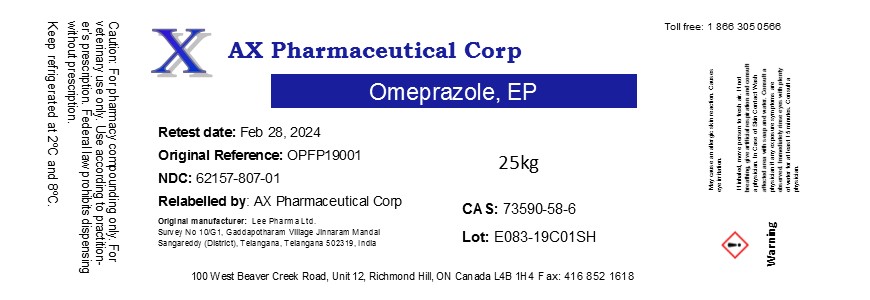 DRUG LABEL: Omeprazole
NDC: 62157-807 | Form: POWDER
Manufacturer: AX Pharmaceutical Corp
Category: other | Type: BULK INGREDIENT
Date: 20190401

ACTIVE INGREDIENTS: OMEPRAZOLE 1 kg/1 kg

Omeprazole